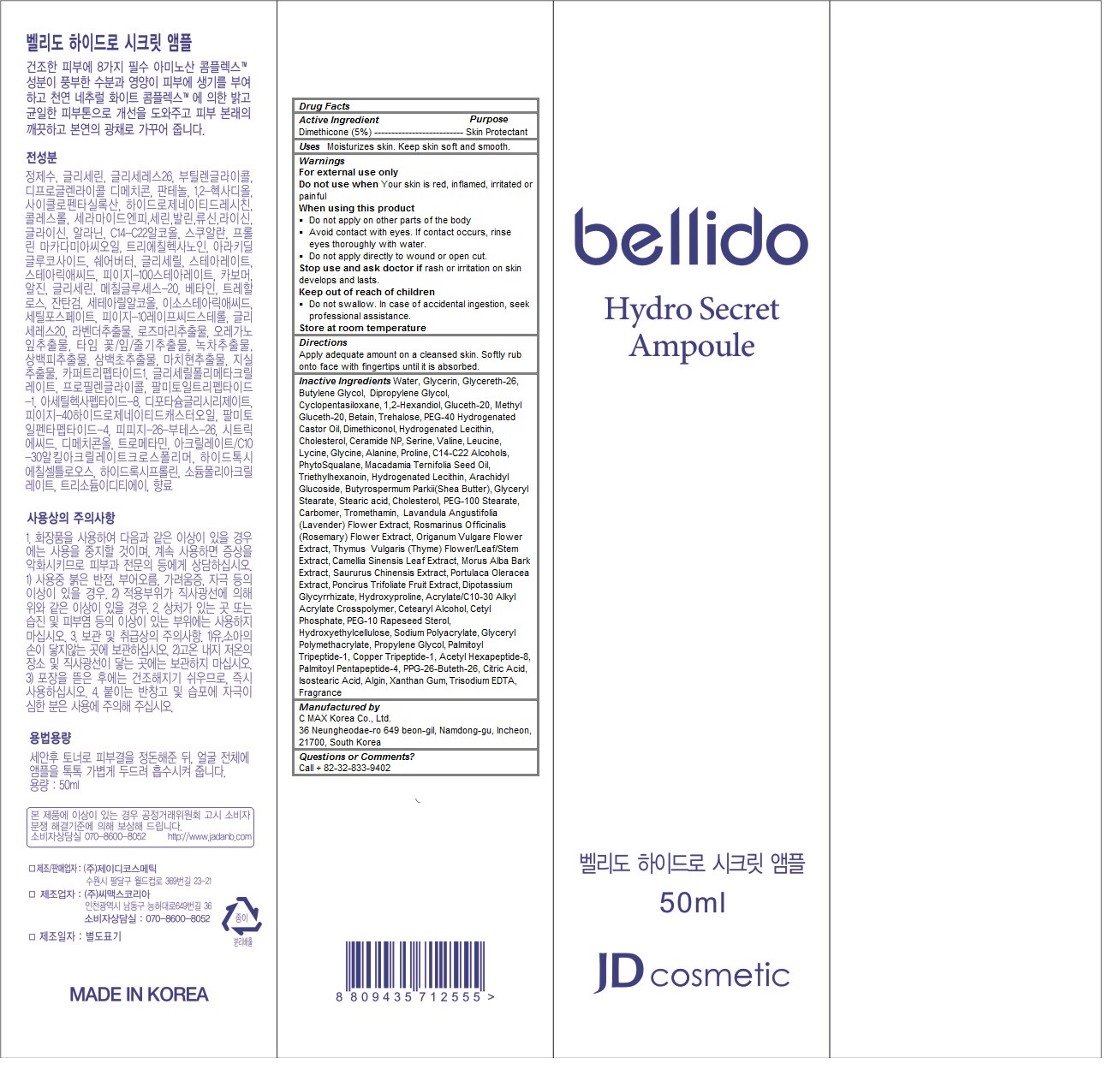 DRUG LABEL: Bellido Hydro Secret Ampoule
NDC: 70949-100 | Form: LIQUID
Manufacturer: C MAX Korea Co., Ltd
Category: otc | Type: HUMAN OTC DRUG LABEL
Date: 20160912

ACTIVE INGREDIENTS: Dimethicone 2.5 g/50 mL
INACTIVE INGREDIENTS: PANTHENOL; WATER; GLYCERIN; Glycereth-26; Butylene Glycol; Dipropylene Glycol; CYCLOMETHICONE 5; 1,2-HEXANEDIOL; METHYL GLUCETH-20; BETAINE; Trehalose; POLYOXYL 40 HYDROGENATED CASTOR OIL; DIMETHICONOL (100000 CST); HYDROGENATED SOYBEAN LECITHIN; Cholesterol; Ceramide NP; Serine; VALINE; LEUCINE; LYSINE; Glycine; Alanine; Proline; C14-22 ALCOHOLS; MACADAMIA OIL; Triethylhexanoin; ARACHIDYL GLUCOSIDE; SHEA BUTTER; GLYCERYL MONOSTEARATE; Stearic acid; PEG-100 Stearate; CARBOXYPOLYMETHYLENE; TROMETHAMINE; LAVANDULA ANGUSTIFOLIA FLOWER; ROSMARINUS OFFICINALIS FLOWER; ORIGANUM VULGARE SUBSP. HIRTUM FLOWER; THYME; GREEN TEA LEAF; MORUS ALBA BARK; PURSLANE; PONCIRUS TRIFOLIATA FRUIT; GLYCYRRHIZINATE DIPOTASSIUM; HYDROXYPROLINE; CARBOMER INTERPOLYMER TYPE A (ALLYL SUCROSE CROSSLINKED); CETYL PHOSPHATE; PEG-10 RAPESEED STEROL; HYDROXYETHYL CELLULOSE (100 MPA.S AT 2%); SODIUM POLYACRYLATE (2500000 MW); Propylene Glycol; PALMITOYL TRIPEPTIDE-1; PREZATIDE COPPER; ACETYL HEXAPEPTIDE-8; PALMITOYL PENTAPEPTIDE-4; PPG-26-BUTETH-26; CITRIC ACID MONOHYDRATE; ISOSTEARIC ACID; SODIUM ALGINATE; Xanthan Gum; EDETATE TRISODIUM

Bellido Hydro Secret Ampoule

Active Ingredients

Dimethicone (5%)

Panthenol (2%)

Purpose

Skin Protectant

Keep out of reach of children

- Do not swallow. In case of accidental ingestion, seek professional assistance.

Warnings

For external use only
Do not use when Your skin is red, inflamed, irritated or painful
When using this product
- Do not apply on other parts of the body
- Avoid contact with eyes. If contact occurs, rinse eyes thoroughly with water.
- Do not apply directly to wound or open cut.
Stop use and ask doctor if rash or irritation on skin develops and lasts.

Store at room temperature

Uses

Moisturizes skin and wrinkle care. Keep skin soft and smooth.

Directions

Apply adequate amount on a cleansed skin. Softly rub onto face with fingertips until it is absorbed.

Inactive Ingredients

Water, Glycerin, Glycereth-26, Butylene Glycol, Dipropylene Glycol, Cyclopentasiloxane, 1,2-Hexandiol, Gluceth-20, Methyl Gluceth-20, Betain, Trehalose, PEG-40 Hydrogenated Castor Oil, Dimethiconol, Dipropylene Glycol, Hydrogenated Lecithin, Cholesterol, Ceramide NP, Serine, Valine, Leucine, Lycine, Glycine, Alanine, Proline, C14-C22 Alcohols, PhytoSqualane, Macadamia Ternifolia Seed Oil, Triethylhexanoin, Hydrogenated Lecithin, Arachidyl Glucoside, Butyrospermum Parkii(Shea Butter), Glyceryl Stearate, Stearic acid, Cholesterol, PEG-100 Stearate, Carbomer, Tromethamin, Lavandula Angustifolia (Lavender) Flower Extract, Rosmarinus Officinalis (Rosemary) Flower Extract, Origanum Vulgare Flower Extract, Thymus Vulgaris (Thyme) Flower/Leaf/Stem Extract, Camellia Sinensis Leaf Extract, Morus Alba Bark Extract, Saururus Chinensis Extract, Portulaca Oleracea Extract, Poncirus Trifoliate Fruit Extract, Dipotassium Glycyrrhizate, Hydroxyproline, Acrylate/C10-30 Alkyl Acrylate Crosspolymer, Cetearyl Alcohol, Cetyl Phosphate, PEG-10 Rapeseed Sterol, Hydroxyethylcellulose, Sodium Polyacrylate, Glyceryl Polymethacrylate, Propylene Glycol, Palmitoyl Tripeptide-1, Copper Tripeptide-1, Acetyl Hexapeptide-8, Palmitoyl Pentapeptide-4, PEG-40 Hydrogenated Castor Oil, PPG-26-Buteth-26, Citric Acid, Isostearic Acid, Algin, Xanthan Gum, Trisodium EDTA, Fragrance